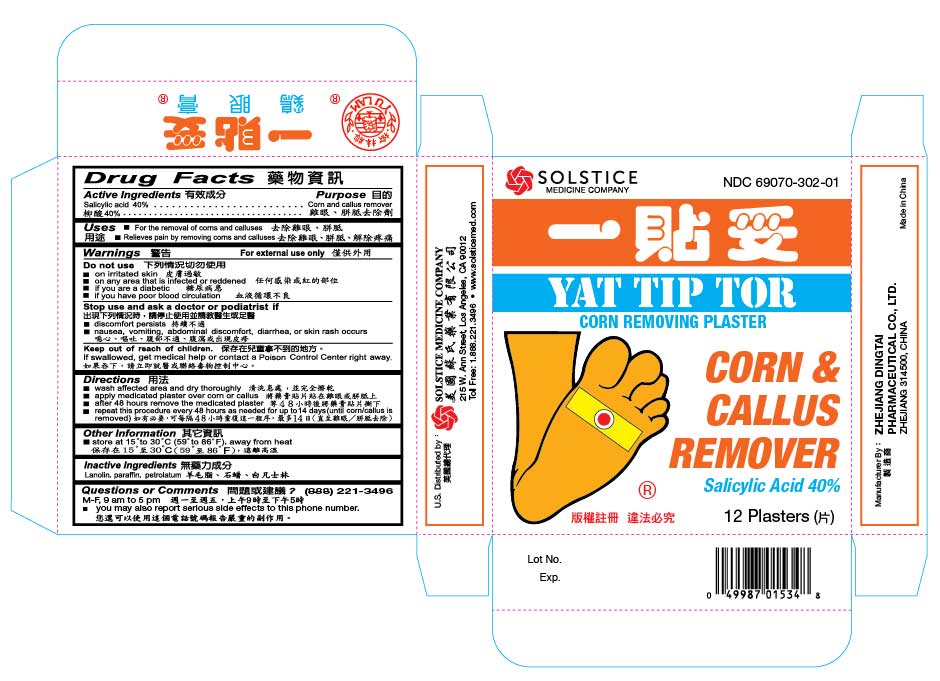 DRUG LABEL: YAT TIP TOR
NDC: 69070-302 | Form: PLASTER
Manufacturer: Zhejiang Dingtai Pharmaceutical Co., Ltd
Category: otc | Type: HUMAN OTC DRUG LABEL
Date: 20251110

ACTIVE INGREDIENTS: SALICYLIC ACID 40 g/1 1
INACTIVE INGREDIENTS: LANOLIN; PARAFFIN; PETROLATUM

Drug Facts

Active Ingredient
Salicylic acid 40%

Purpose
Corn and callus remover

Uses
For the removal of corns and calluses
Relieves pain by removing corns and calluses

Warnings
For external use only
Allergy alert: This product contains natural rubber latex which may cause allergic reactions

Do not use
on irritated skin
on any area that is infected or reddened
if you are a diabetic
if you have poor blood circulation

Stop use and ask a doctor or podiatrist if
discomfort persists
nausea, vomiting, abdominal discomfort, diarrhea, or skin rash occurs

Keep out of reach of children.If swallowed, get medical help or contact an Poison Control Center right away.

Directions
wash affected area and dry thoroughly
apply medicated plaster over corn or callus
after 48 hours remove the medicated plaster
repeat this procedure every 48 hours as needed for up to 14 days (until corn/callus is removed)

Other Information
store at 15∞ to 30 C (59 to 86 F), away from heat

Inactive Ingredients Lanolin, paraffin, petrolatum.

Questions or Comments?(888) 221-3496 M-F 9am to 5pm

PACKAGE LABEL

Yat Tip Tor

Corn & Callus Remover

Salicylic acid 40%

NDC 69070-302-01

12 Plasters